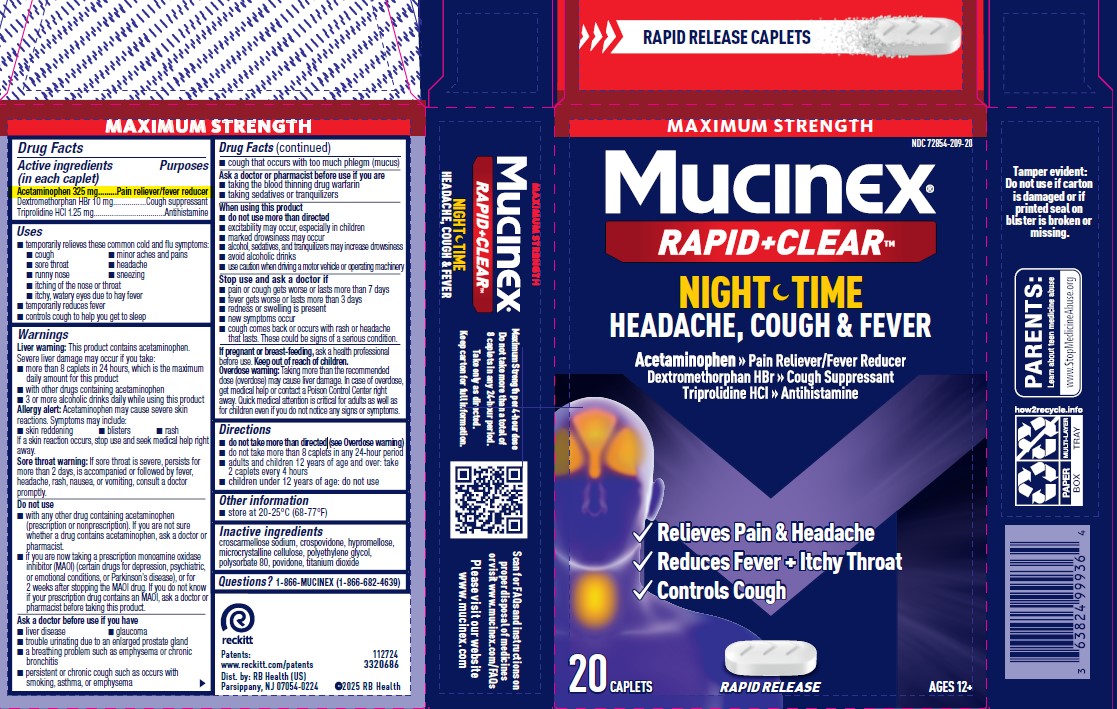 DRUG LABEL: Mucinex Nightshift Sinus
NDC: 72854-209 | Form: TABLET, COATED
Manufacturer: RB Health (US) LLC
Category: otc | Type: HUMAN OTC DRUG LABEL
Date: 20250515

ACTIVE INGREDIENTS: DEXTROMETHORPHAN HYDROBROMIDE 10 mg/1 1; ACETAMINOPHEN 325 mg/1 1; TRIPROLIDINE HYDROCHLORIDE 1.25 mg/1 1
INACTIVE INGREDIENTS: HYPROMELLOSE, UNSPECIFIED; TITANIUM DIOXIDE; MICROCRYSTALLINE CELLULOSE; POLYETHYLENE GLYCOL, UNSPECIFIED; CROSCARMELLOSE SODIUM; POVIDONE, UNSPECIFIED; POLYSORBATE 80; CROSPOVIDONE, UNSPECIFIED

Mucinex Rapid+Clear Nighttime Headache, Cough & Fever

Active ingredients
(in each caplet)

Acetaminophen 325 mg
Dextromethorphan HBr 10 mg
Triprolidine HCl 1.25 mg

Uses
■ temporarily relieves these common cold and flu symptoms:
■ cough ■ minor aches and pains
■ sore throat ■ headache
■ runny nose ■ sneezing
■ itching of the nose or throat
■ itchy, watery eyes due to hay fever
■ temporarily reduces fever
■ controls cough to help you get to sleep

Warnings
Liver warning: This product contains acetaminophen.
Severe liver damage may occur if you take:
■ more than 8 caplets in 24 hours, which is the maximum
daily amount for this product
■ with other drugs containing acetaminophen
■ 3 or more alcoholic drinks daily while using this product
Allergy alert: Acetaminophen may cause severe skin
reactions. Symptoms may include:
■ skin reddening ■ blisters ■ rash
If a skin reaction occurs, stop use and seek medical help right
away.

Sore throat warning: If sore throat is severe, persists for
more than 2 days, is accompanied or followed by fever,
headache, rash, nausea, or vomiting, consult a doctor
promptly.

Do not use
■ with any other drug containing acetaminophen
(prescription or nonprescription). If you are not sure
whether a drug contains acetaminophen, ask a doctor or
pharmacist.
■ if you are now taking a prescription monoamine oxidase
inhibitor (MAOI) (certain drugs for depression, psychiatric,
or emotional conditions, or Parkinson’s disease), or for
2 weeks after stopping the MAOI drug. If you do not know
if your prescription drug contains an MAOI, ask a doctor or
pharmacist before taking this product.

Ask a doctor before use if you have
■ liver disease ■ glaucoma
■ trouble urinating due to an enlarged prostate gland
■ a breathing problem such as emphysema or chronic
bronchitis
■ persistent or chronic cough such as occurs with
smoking, asthma, or emphysema

■ cough that occurs with too much phlegm (mucus)

Ask a doctor or pharmacist before use if you are
■ taking the blood thinning drug warfarin
■ taking sedatives or tranquilizers
When using this product
■ do not use more than directed
■ excitability may occur, especially in children
■ marked drowsiness may occur
■ alcohol, sedatives, and tranquilizers may increase drowsiness
■ avoid alcoholic drinks
■ use caution when driving amotor vehicle or operatingmachinery
Stop use and ask a doctor if
■ pain or cough gets worse or lasts more than 7 days
■ fever gets worse or lasts more than 3 days
■ redness or swelling is present
■ new symptoms occur
■ cough comes back or occurs with rash or headache
that lasts. These could be signs of a serious condition.

Overdose warning: Taking more than the recommended
dose (overdose) may cause liver damage. In case of overdose,
get medical help or contact a Poison Control Center right
away. Quick medical attention is critical for adults as well as
for children even if you do not notice any signs or symptoms.

Directions
■ do not take more than directed (see Overdose warning)
■ do not take more than 8 caplets in any 24-hour period
■ adults and children 12 years of age and over: take
2 caplets every 4 hours
■ children under 12 years of age: do not use

Other information
■ store at 20-25°C (68-77°F)

Questions? 1-866-MUCINEX
(1-866-682-4639)

Inactive ingredients
croscarmellose sodium, crospovidone, hypromellose,
microcrystalline cellulose, polyethylene glycol,
polysorbate 80, povidone, titanium dioxide

PURPOSE

Acetaminophen 325 mg ........ Pain reliever/fever reducer
Dextromethorphan HBr 10 mg................Cough suppressant
Triprolidine HCl 1.25 mg...................................Antihistamine

Keep out of reach of children.